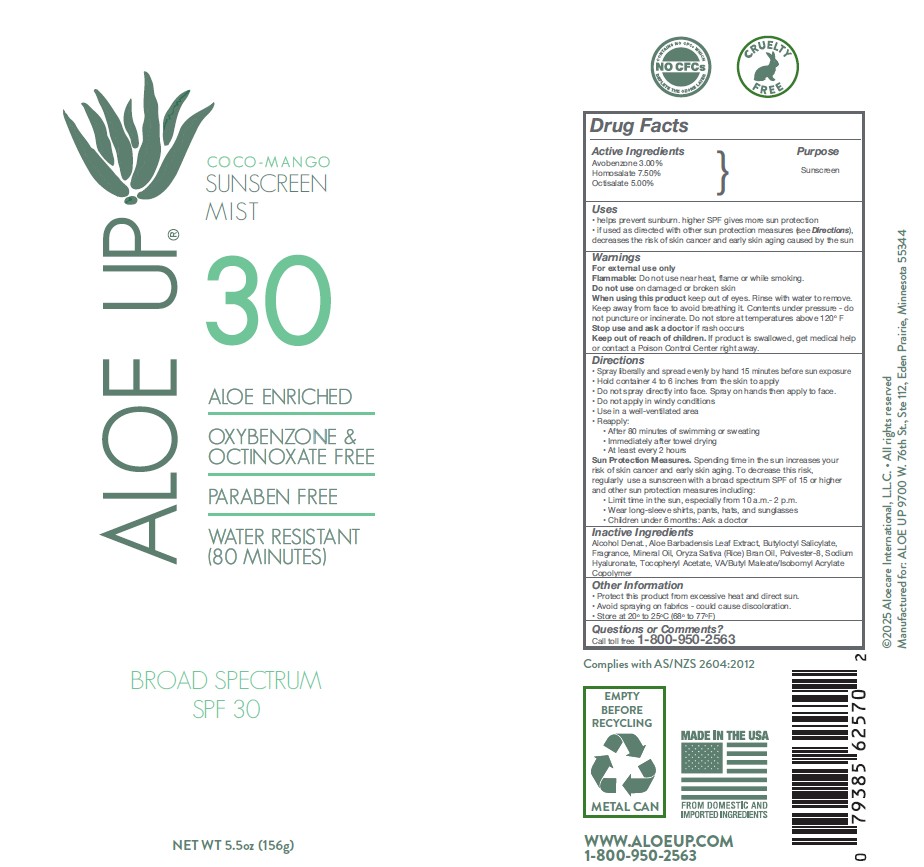 DRUG LABEL: Aloe Up SPF 30 coco-mango mist
NDC: 61477-237 | Form: SPRAY
Manufacturer: Aloe Up
Category: otc | Type: HUMAN OTC DRUG LABEL
Date: 20250924

ACTIVE INGREDIENTS: AVOBENZONE 3 g/100 g; HOMOSALATE 7.5 g/100 g; OCTISALATE 5 g/100 g
INACTIVE INGREDIENTS: ALCOHOL; ALOE; BUTYLOCTYL SALICYLATE; FRAGRANCE LY-11285; MINERAL OIL; ORYZA SATIVA (RICE) BRAN; SODIUM HYALURONATE; .ALPHA.-TOCOPHEROL ACETATE

Aloe Up SPF 30 coco-mango spray

Active ingredienta

Avobenzone 3.0%, Homosalate 7.5%, Octisalate 5.0%

Uses

• helps prevent sunburn. higher SPF gives more sun protection
• if used as directed with other sun protection measures (see Directions),
decreases the risk of skin cancer and early skin aging caused by the sun

Direction

• Spray liberally and spread evenly by hand 15 minutes before sun exposure
• Hold container 4 to 6 inches from the skin to apply
• Do not spray directly into face. Spray on hands then apply to face.
• Do not apply in windy conditions
• Use in a well-ventilated area
• Reapply:
• After 80 minutes of swimming or sweating
• Immediately after towel drying
• At least every 2 hours
Sun Protection Measures. Spending time in the sun increases your
risk of skin cancer and early skin aging. To decrease this risk,
regularly use a sunscreen with a broad spectrum SPF of 15 or higher
and other sun protection measures including:
• Limit time in the sun, especially from 10 a.m.- 2 p.m.
• Wear long-sleeve shirts, pants, hats, and sunglasses
• Children under 6 months: Ask a doctor

Warnings

For external use only
Flammable: Do not use near heat, flame or while smoking.
Do not useon damaged or broken skin
When using this productkeep out of eyes. Rinse with water to remove.
Keep awayfrom face to avoid breathing it. Contents under pressure - do
not puncture or incinerate. Do not storeat temperatures above 120o F
Stop use and ask a doctor ifrash occurs

Keep out of reach of children.

If product is swallowed, get medical help or contact a Poison Control Center right away.

Inactive Ingredients

Alcohol Denat., Aloe Barbadensis Leaf Extract, Butyloctyl Salicylate, Fragrance, Mineral Oil, Oryza Sativa (Rice) Bran Oil, Polvester-8, Sodium
Hyaluronate, Tocopheryl Acetate

Other Information

• Protect this product from excessive heat and direct sun.
• Avoid spraying on fabrics - could cause discoloration.
• Store at 20o to 25oC (68F to 77F)